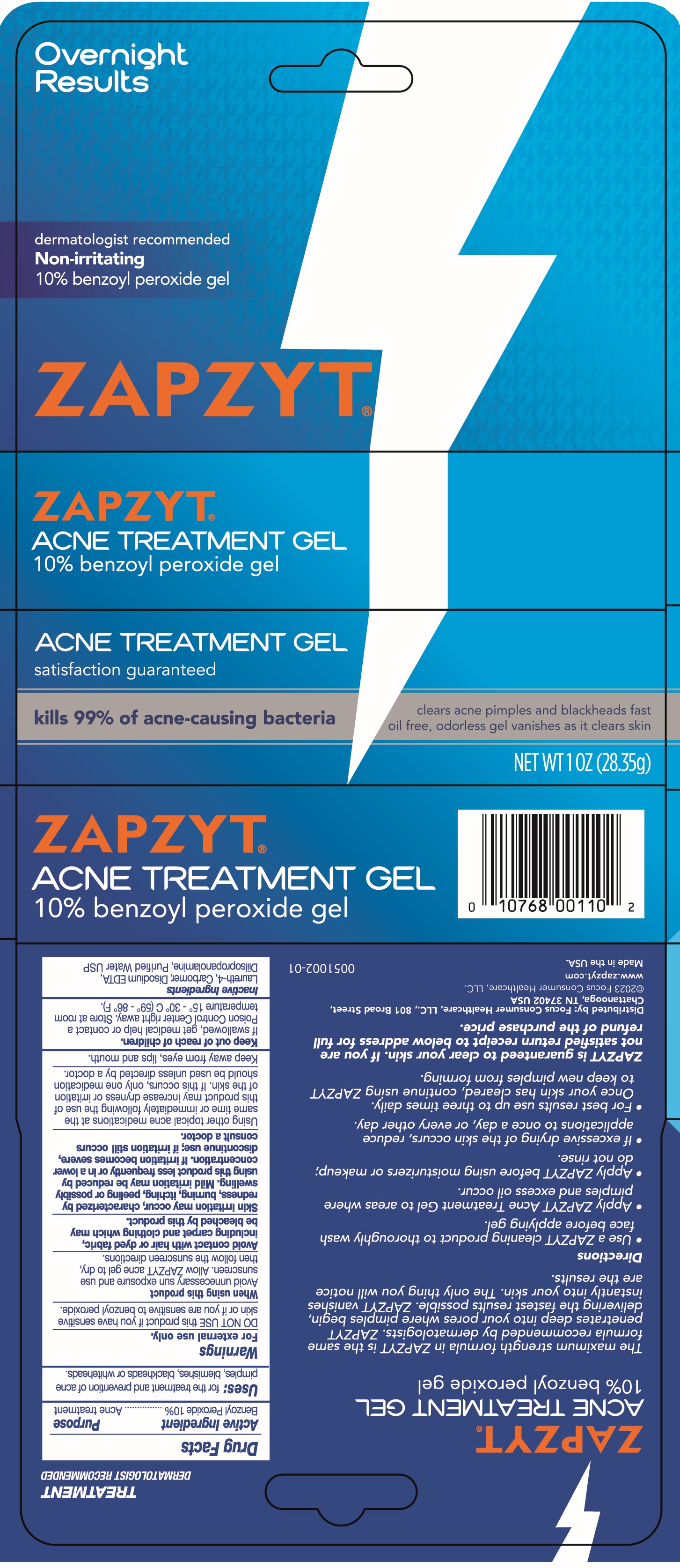 DRUG LABEL: Zapzyt Acne Treatment Gel
NDC: 71687-0011 | Form: GEL
Manufacturer: Focus Consumer Healthcare, LLC
Category: otc | Type: HUMAN OTC DRUG LABEL
Date: 20250212

ACTIVE INGREDIENTS: BENZOYL PEROXIDE 10 g/100 g
INACTIVE INGREDIENTS: WATER; DIISOPROPANOLAMINE; LAURETH-4; CARBOMER 980; EDETATE DISODIUM

Zapzyt Acne Treatment Gel

ACTIVE INGREDIENT

Benzoyl Peroxide 10%

PURPOSE

Acne treatment

Uses

for the treatment and prevention of acne pimples, blemishes, blackheads or whiteheads

Warnings

For external use only.

DO NOT USE this product if you have sensitive skin or if you are sensitive to benzoyl peroxide

When using this product

Avoid unnecessary sun exposure and use sunscreen. Allow ZAPZYT acne gel to dry, then follow the sunscreen directions.

Avoid contact with hair or dyed fabric, including carpet and clothing which may be bleached by this product.

Skin irritation may occur, characterized by redness, burning, itching, peeling or possibly swelling. Mild irritation may be reduced by using this product less frequently or in a lower concentration. If irritation becomes severe, discontinue use; if irritation still occurs consult a doctor.

Using other topical acne medications at the same time or immediately following the use of this product may increase dryness or irritation of the skin. If this occurs, only one medication should be used unless directed by a doctor.

Keep away from eyes, lips and mouth

OTC - Keep out of Reach of Children

If swallowed, get medical help or contact a Poison Control Center right away. Store at room temperature 15-30 degrees C (59-86 degrees F).

Directions

Use a ZAPZYT cleaning product to thoroughly wash face before applying gel.

Apply ZAPZYT Acne Treatment Gel to areas where pimples and excess oil occur

Apply ZAPZYT before using moisturizer or makeup; do not rinse.

If excessive drying of the skin occurs, reduce applications to once a day, or every other day.

For best results use up to three tiimes daily. Once your skin has cleared, continue using ZAPZYT to keep new pimples from forming

Inactive ingredients

Laureth-4, Carbomer, Disodium EDTA, Dilsopropanolamine, Purified Water USP

PACKAGE LABEL

Zapzyt Acne Treatment Gel

10% benzoyl peroxide get

kills 99% of acne-causing bacteria

clears acne pinples and blackheads fast

oil free, odorless gel vanishes as it clears skin